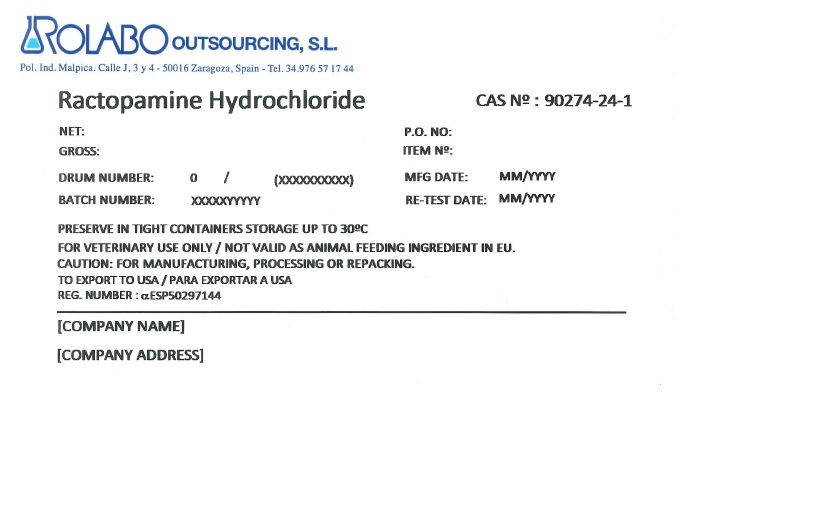 DRUG LABEL: RACTOPAMINE HYDROCHLORIDE
NDC: 63827-1016 | Form: POWDER
Manufacturer: Rolabo Outsourcing, S.L.
Category: other | Type: BULK INGREDIENT - ANIMAL DRUG
Date: 20231101

ACTIVE INGREDIENTS: RACTOPAMINE HYDROCHLORIDE 1 kg/1 kg

Ractopamine Hydrochloride

PACKAGE LABEL

ROLABO OUTSOURCING, S.L.

Pol. Ind. Malpica. Calle J, 3 y 4 - 50016 Zaragoza, Spain - Tel. 34.976 57 17 44

RACTOPAMINE HYDROCHLORIDE

CAS NUMBER: 90274-24-1

PRESERVE IN TIGHT CONTAINERS STORAGE UP TO 30°C

FOR VETERINARY USE ONLY / NOT VALID AS ANIMAL FEEDING INGREDIENT IN EU

CAUTION: FOR MANUFACTURING, PROCESSING OR REPACKING

TO EXPORT TO USA / PARA EXPORTAR A USA

REG. NUMBER: αESP50297144